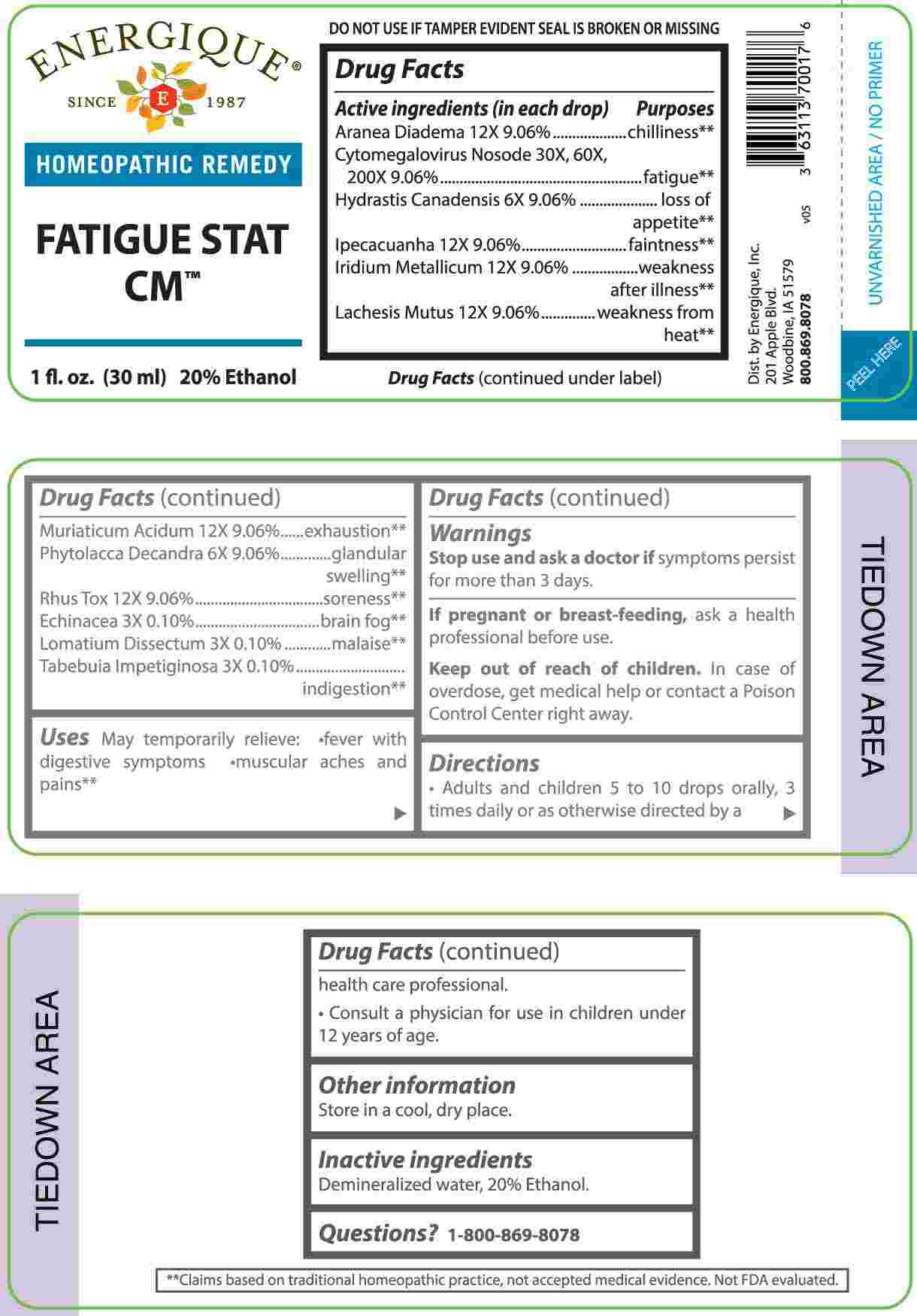 DRUG LABEL: Fatigue Stat CM
NDC: 44911-0609 | Form: LIQUID
Manufacturer: Energique, Inc
Category: homeopathic | Type: HUMAN OTC DRUG LABEL
Date: 20240508

ACTIVE INGREDIENTS: ECHINACEA ANGUSTIFOLIA WHOLE 3 [hp_X]/1 mL; LOMATIUM DISSECTUM ROOT 3 [hp_X]/1 mL; TABEBUIA IMPETIGINOSA BARK 3 [hp_X]/1 mL; GOLDENSEAL 3 [hp_X]/1 mL; PHYTOLACCA AMERICANA ROOT 6 [hp_X]/1 mL; ARANEUS DIADEMATUS 6 [hp_X]/1 mL; IPECAC 12 [hp_X]/1 mL; IRIDIUM 12 [hp_X]/1 mL; LACHESIS MUTA VENOM 12 [hp_X]/1 mL; HYDROCHLORIC ACID 12 [hp_X]/1 mL; TOXICODENDRON PUBESCENS LEAF 12 [hp_X]/1 mL; HUMAN HERPESVIRUS 5 30 [hp_X]/1 mL
INACTIVE INGREDIENTS: WATER; ALCOHOL

DRUG FACTS:

ACTIVE INGREDIENTS:

Aranea Diadema 12X 9.06%, Cytomegalovirus Nosode 30X, 60X, 200X 9.06%, Hydrastis Canadensis 6X 90.6%, Ipecacuanha 12X 9.06%, Iridium Metallicum 12X 9.06%, Lachesis Mutus 12X 9.06%, Muriaticum Acidum 12X 9.06%, Phytolacca Decandra 6X 9.06%, Rhus Tox 12X 9.06%; Echinacea 3X 0.10%, Lomatium Dissectum 3X 0.10%, Tabebuia Impetiginosa 3X 0.10%.

PURPOSE:

Aranea Diadema - chilliness,** Cytomegalovirus Nosode - fatigue,** Hydrastis Canadensis – loss of appetite,** Ipecacuanha - faintness,** Iridium Metallicum – weakness after illness,** Lachesis Mutus – weakness from heat,** Muriaticum Acidum - exhaustion,** Phytolacca Decandra – glandular swelling,** Rhus Tox – soreness, ** Echinacea – brain fog,** Lomatium Dissectum - malaise, Tabebuia Impetiginosa – indigestion**

**Claims based on traditional homeopathic practice, not accepted medical evidence. Not FDA evaluated.

USES:

May temporarily relieve:

• fever with digestive symptoms

• muscular aches and pains**

**Claims based on traditional homeopathic practice, not accepted medical evidence. Not FDA evaluated.

WARNINGS:

Stop use and ask a doctor if symptoms persist for more than 3 days.

If pregnant or breast-feeding, ask a health professional before use.

Keep out of reach of children. In case of overdose, get medical help or contact a Poison Control Center right away.

DO NOT USE IF TAMPER EVIDENT SEAL IS BROKEN OR MISSING.

Store in a cool, dry place.

KEEP OUT OF REACH OF CHILDREN:

In case of overdose, get medical help or contact a Poison Control Center right away.

DIRECTIONS:

• Adults and children 5 to 10 drops orally, 3 times daily or as otherwise directed by a health care professional.

• Consult a physician for use in children under 12 years of age.

INACTIVE INGREDIENTS:

Demineralized water, 20% Ethanol.

QUESTIONS:

Dist. by Energique, Inc.

201 Apple Blvd.

Woodbine, IA 51579

800.869.8078

PACKAGE LABEL DISPLAY:

ENERGIQUE
SINCE 1987
HOMEOPATHIC REMEDY
FATIGUE STAT CM
1 fl. oz. (30 ml)